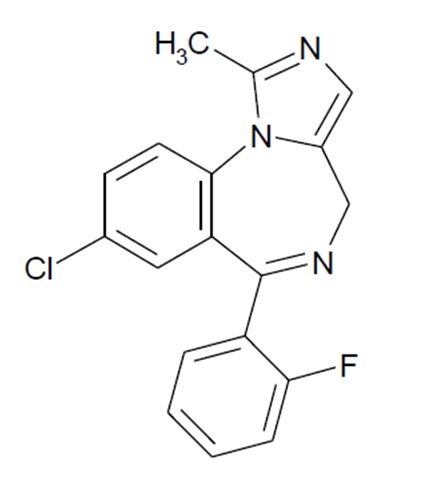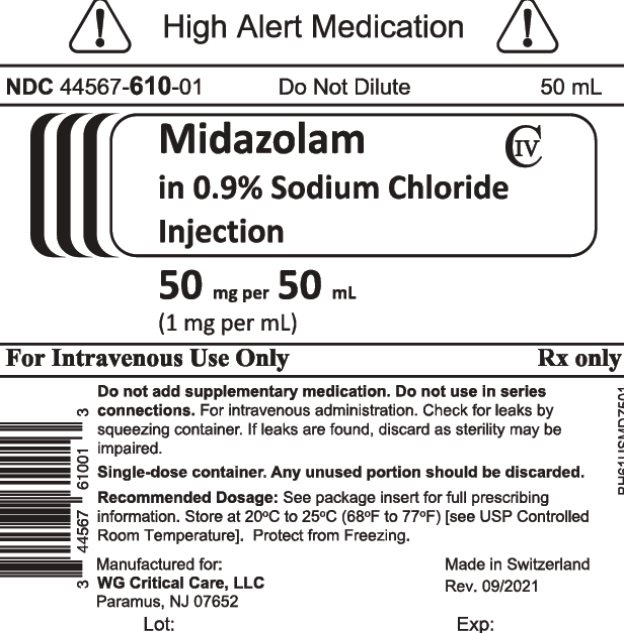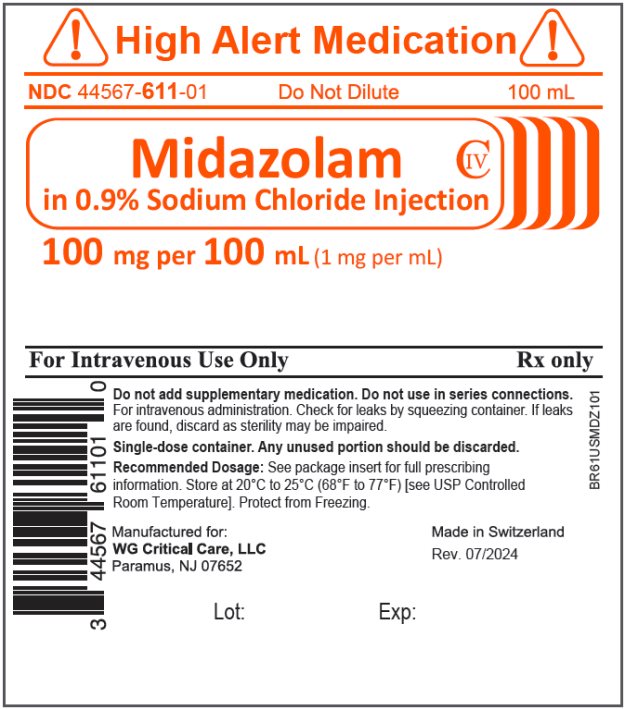 DRUG LABEL: Midazolam in Sodium Chloride
NDC: 44567-610 | Form: INJECTION, SOLUTION
Manufacturer: WG Critical Care, LLC.
Category: prescription | Type: HUMAN PRESCRIPTION DRUG LABEL
Date: 20240630
DEA Schedule: CIV

ACTIVE INGREDIENTS: MIDAZOLAM 1 mg/1 mL
INACTIVE INGREDIENTS: SODIUM CHLORIDE 9 mg/1 mL; HYDROCHLORIC ACID; SODIUM HYDROXIDE

HIGHLIGHTS OF PRESCRIBING INFORMATION

These highlights do not include all the information needed to use Midazolam Injection safely and effectively. See full prescribing information for Midazolam Injection.
MIDAZOLAM IN SODIUM CHLORIDE injection, for intravenous use, CIV
Initial U.S. Approval: 1985

WARNING: PERSONNEL AND EQUIPMENT FOR MONITORING AND RESUSCITATION, AND RISKS FROM CONCOMITANT USE WITH OPIOID ANALGESICS AND OTHER SEDATIVE-HYPNOTICS Personnel and Equipment for Monitoring and ResuscitationOnly personnel trained in the administration of procedural sedation, and not involved in the conduct of the diagnostic or therapeutic procedure, should administer Midazolam in 0.9% Sodium Chloride Injection [see Dosage and Administration (2.1), Warnings and Precautions (5.1)].Administering personnel must be trained in the detection and management of airway obstruction, hypoventilation, and apnea, including the maintenance of a patent airway, supportive ventilation, and cardiovascular resuscitation [see Dosage and Administration (2.1), Warnings and Precautions (5.1)].Resuscitative drugs, and age- and size-appropriate equipment for bag/valve/mask assisted ventilation must be immediately available during administration of Midazolam in 0.9% Sodium Chloride Injection [see Dosage and Administration (2.1), Warnings and Precautions (5.1)].Continuously monitor vital signs during sedation and during the recovery period [see Dosage and Administration (2.1), Warnings and Precautions (5.1)].Risks from Concomitant Use with Opioid Analgesics and Other Sedative HypnoticsConcomitant use of benzodiazepines, including Midazolam in 0.9% Sodium Chloride Injection, and opioids may result in profound sedation, respiratory depression, coma, and death. Continuously monitor patients for respiratory depression and depth of sedation [see Warnings and Precautions (5.2) andDrug Interaction (7.1)].

WARNING: PERSONNEL AND EQUIPMENT FOR MONITORING AND RESUSCITATION, AND RISKS FROM CONCOMITANT USE WITH OPIOID ANALGESICS AND OTHER SEDATIVE-HYPNOTICS

See full prescribing information for complete boxed warning.

- Only personnel trained in the administration of procedural sedation, and not involved in the conduct of the diagnostic or therapeutic procedure, should administer Midazolam Injection. (Error! Hyperlink reference not valid., Error! Hyperlink reference not valid.)
- Administering personnel must be trained in the detection and management of airway obstruction, hypoventilation, and apnea, including the maintenance of a patent airway, supportive ventilation, and cardiovascular resuscitation. (Error! Hyperlink reference not valid., Error! Hyperlink reference not valid.)
- Resuscitative drugs, and age- and size-appropriate equipment for bag/valve/mask assisted ventilation must be immediately available during administration of Midazolam Injection. (Error! Hyperlink reference not valid., Error! Hyperlink reference not valid.)
- Continuously monitor vital signs during sedation and through the recovery period. (Error! Hyperlink reference not valid., Error! Hyperlink reference not valid.)
- Concomitant use of benzodiazepines with opioid analgesics may result in profound sedation, respiratory depression, coma, and death. Continuously monitor patients for respiratory depression and depth of sedation. (Error! Hyperlink reference not valid., Error! Hyperlink reference not valid.)

1 INDICATIONS AND USAGE

Midazolam in 0.9% Sodium Chloride Injection is a benzodiazepine indicated for:

- continuous intravenous infusion for sedation of intubated and mechanically ventilated adult, pediatric, and neonatal patients as a component of anesthesia or during treatment in a critical care setting. (1)

2 DOSAGE AND ADMINISTRATION

- For intravenous injection only. Avoid intra-arterial injection or extravasation. (2.1)
- Individualize dosing and titrate to desired clinical response, taking into account patient age, clinical status, and concomitant use of other CNS depressants. (2.1)
- See Full Prescribing Information for complete dosage and administration information. (2)

3 DOSAGE FORMS AND STRENGTHS

Injection: 50 mg per 50 mL (1mg/mL) and 100 mg per 100 mL (1 mg/mL) in single-dose bags. (3)

4 CONTRAINDICATIONS

Midazolam in 0.9% Sodium Chloride Injection is contraindicated in patients with:

- known hypersensitivity to midazolam. (4)
- acute narrow-angle glaucoma. (4)

5 WARNINGS AND PRECAUTIONS

Cardiorespiratory Adverse Reactions: Serious cardiorespiratory adverse reactions have occurred, sometimes resulting in death or permanent neurologic injury. (5.3)

Paradoxical Behavior: Agitation, involuntary movements (including tonic/clonic movements and muscle tremor), hyperactivity and combativeness have been reported in both adult and pediatric patients. (5.4)

Dependence and Withdrawal with Long-Term Use: Use for several days to weeks may lead to physical dependence to midazolam. Do not abruptly discontinue midazolam. Gradually taper the dosage using a tapering schedule that is individualized to the patient. (5.5)

Debilitation and Comorbid Considerations: Higher risk adult and pediatric surgical patients, elderly patients and debilitated adult and pediatric patients require lower dosages, whether or not concomitant sedating medications have been administered. (5.6)

Risk of Intra-Arterial Injection: There have been limited reports of intra-arterial injection of midazolam. Adverse events have included local reactions, as well as isolated reports of seizure activity in which no clear causal relationship was established. (5.7)

Impaired Cognitive Function: Because of partial or complete impairment of recall, patients should not operate hazardous machinery or a motor vehicle until drug effects have subsided. (5.8)

Hypotension and Seizure in Preterm Infants and Neonates: Avoid rapid injection in the neonatal population. (5.9)

Neonatal Sedation and Withdrawal Syndrome: Receiving Midazolam in 0.9% Sodium Chloride Injection during pregnancy can result in neonatal sedation and/or neonatal withdrawal. (5.10, 8.1)

Pediatric Neurotoxicity: In developing animals, exposures greater than 3 hours cause neurotoxicity. Weigh benefits against potential risks when considering elective procedures in children under 3 years old. (5.11)

6 ADVERSE REACTIONS

The most common adverse reactions (≥15%) were decreased tidal volume, decreased respiratory rate, and apnea. (6)

To report SUSPECTED ADVERSE REACTIONS, contact WG Critical Care, LLC at 1-866-562-4708 or FDA at 1-800-FDA-1088 or www.fda.gov/medwatch.

7 DRUG INTERACTIONS

Opioid Analgesics and Other Sedative Hypnotics: Risk of respiratory depression is increased (7.1)

Cytochrome P450-3A4 Inhibitors: May result in prolonged sedation due to decreased plasma clearance of midazolam. (7.2)

8 USE IN SPECIFIC POPULATIONS

Lactation: A lactating woman may pump and discard breast milk for 4 to 8 hours after treatment with midazolam (8.2).

FULL PRESCRIBING INFORMATION

1 INDICATIONS AND USAGE

Midazolam in 0.9% Sodium Chloride Injection is indicated:

- Continuous intravenous infusion for sedation of intubated and mechanically ventilated adult, pediatric, and neonatal patients as a component of anesthesia or during treatment in a critical care setting.

2 DOSAGE AND ADMINISTRATION

2.1 Important Dosage and Administration Instructions

- Midazolam in 0.9% Sodium Chloride Injection should only be administered intravenously. Avoid intra-arterial injection or extravasation [see Warnings and Precautions (5.7)].
- Only personnel trained in the administration of procedural sedation, and not involved in the conduct of the diagnostic or therapeutic procedure, should administer Midazolam in 0.9% Sodium Chloride Injection.
- Administering personnel must be trained in the detection and management of airway obstruction, hypoventilation, and apnea, including the maintenance of a patent airway, supportive ventilation, and cardiovascular resuscitation.
- Supplemental oxygen, resuscitative drugs, and age‑ and size-appropriate equipment for bag/valve/mask assisted ventilation must be immediately available during administration of Midazolam in 0.9% Sodium Chloride Injection. A benzodiazepine reversal agent should be immediately available.
- Continuously monitor vital signs during sedation and through the recovery period [see Error! Hyperlink reference not valid.].

Midazolam must never be used without individualization of dosage particularly when used with other medications capable of producing central nervous system depression [Warnings and Precautions (5.2)].

Midazolam in 0.9% Sodium Chloride Injection can cause respiratory depression. It is a potent sedative agent that requires slow administration and individualization of dosage. Excessive single doses or rapid intravenous administration may result in respiratory depression, airway obstruction and/or arrest. Continuously monitor patients for early signs of hypoventilation, airway obstruction, and apnea using capnography, pulse oximetry, and clinical assessment [see Warnings and Precautions (5.3)].

Reactions such as agitation, involuntary movements, hyperactivity and combativeness have been reported in adult and pediatric patients. Should such reactions occur, the response to each dose of midazolam and all other drugs, including local anesthetics, should be evaluated before proceeding. Reversal of such responses with flumazenil has been reported in pediatric patients [see Warnings and Precautions (5.4)].

Visually inspect parenteral drug products for particulate matter and discoloration prior to administration, whenever solution and container permit. If solution is discolored or particulate matter is present, do not use.

2.2 General Dosing Information

Individualize dosing and titrate to desired clinical response, taking into account patient age, clinical status, and concomitant use of other CNS depressants. Titrate to effect with multiple small doses while continuously monitoring respiratory and cardiac function (i.e., pulse oximetry). To minimize the potential for oversedation, allow adequate time between doses to achieve peak central nervous system effect (3 to 5 minutes).

Adults and Pediatrics:

Sedation guidelines recommend a careful presedation history to determine how a patient's underlying medical conditions or concomitant medications might affect their response to sedation/analgesia as well as a physical examination including a focused examination of the airway for abnormalities. Further recommendations include appropriate presedation fasting.

Pediatrics:

Pediatric patients generally require higher dosages of midazolam (mg/kg) than adults. For deeply sedated pediatric patients a dedicated individual, other than the practitioner performing the procedure, should monitor the patient throughout the procedure.

Elderly and Debilitated Patients

Intravenous doses of midazolam should be decreased for elderly and for debilitated patients [see Warnings and Precautions (5.6)]. These patients will also probably take longer to recover completely after midazolam administration for the induction of anesthesia [see Warnings and Precautions (5.8)].

Monitoring

Patient response to sedative agents, and resultant respiratory status, is variable. Regardless of the intended level of sedation or route of administration, sedation is a continuum; a patient may move easily from light to deep sedation, with potential loss of protective reflexes. This is especially true in pediatric patients. Continuously monitor vital signs during sedation and through the recovery period [see Error! Hyperlink reference not valid.].

2.3 Dosing Recommendations

Table 1 provides dosing recommendations for adult, pediatric, and neonatal patients.

Table 1. Dosing Recommendations for Continuous Intravenous Infusion in Adult, Pediatric, and Neonatal Patients

ADULT PATIENTS | If a loading dose is necessary to rapidly initiate sedation, 0.01 mg/kg to 0.05 mg/kg (approximately 0.5 mg to 4 mg for a typical adult) may be given slowly or infused over several minutes. This dose may be repeated at 10 to 15 minute intervals until adequate sedation is achieved. For maintenance of sedation, the usual initial infusion rate is 0.02 mg/kg/hr to 0.10 mg/kg/hr (1 mg/hr to 7 mg/hr). Higher loading or maintenance infusion rates may occasionally be required in some patients. Use the lowest recommended doses in patients with residual effects from anesthetic drugs, or in those concurrently receiving other sedatives or opioids.; Individual response to midazolam is variable. Titrate the infusion rate to the desired level of sedation, taking into account the patient's age, clinical status and current medications. In general, midazolam should be infused at the lowest rate that produces the desired level of sedation. Assess sedation at regular intervals and adjust the midazolam infusion rate. Finding the minimum effective infusion rate decreases the potential accumulation of midazolam and provides for the most rapid recovery once the infusion is terminated.
PEDIATRIC PATIENTS | UNLIKE ADULT PATIENTS, PEDIATRIC PATIENTS GENERALLY RECEIVE INCREMENTS OF MIDAZOLAM ON A MG/KG BASIS. As a group, pediatric patients generally require higher dosages of midazolam (mg/kg) than adults. Younger (less than six years) pediatric patients may require higher dosages (mg/kg) than older pediatric patients. In obese pediatric patients, calculate the dose based on ideal body weight.; Titrate the dose to the desired level of sedation. Assess for desired level of sedation and vital signs at regular intervals.
PRETERM AND TERM NEONATAL PATIENTS | Based on pharmacokinetic parameters and reported clinical experience in preterm and term neonates WHOSE TRACHEA WAS INTUBATED, initiate continuous intravenous infusions of Midazolam in Sodium Chloride Injection at a rate of 0.03 mg/kg/hr (0.5 mcg/kg/min) in neonates <32 weeks and 0.06 mg/kg/hr (1 mcg/kg/min) in neonates >32 weeks. Intravenous loading doses should not be used in neonates, rather the infusion may be run more rapidly for the first several hours to establish therapeutic plasma levels. Frequently assess the rate of infusion, particularly after the first 24 hours so as to administer the lowest possible effective dose and reduce the potential for drug accumulation. Hypotension may be observed in patients who are critically ill and in preterm and term infants, particularly those receiving fentanyl and/or when midazolam is administered rapidly.; When sedating preterm and former preterm neonates WHOSE TRACHEA WAS NOT INTUBATED, monitor respiratory parameters due to an increased risk of apnea.

2.4 Safe Discontinuation of Midazolam in 0.9% Sodium Chloride Injection After Long-Term Use

If Midazolam in 0.9% Sodium Chloride Injection is administered long-term (for several days to weeks), do not abruptly discontinue. Gradually taper the dosage in physically-dependent patients using a tapering schedule that is individualized to the patient. (see Warnings and Precautions (5.5).

3 DOSAGE FORMS AND STRENGTHS

Midazolam in 0.9% Sodium Chloride Injection, 50 mg per 50 mL (1 mg/mL) and 100 mg per 100 mL (1 mg/ mL), is a clear, colorless solution supplied in single-dose bags with an aluminum overwrap.

4 CONTRAINDICATIONS

Midazolam in 0.9% Sodium Chloride Injection is contraindicated in patients with:

- Known hypersensitivity to midazolam
- Acute narrow-angle glaucoma

5 WARNINGS AND PRECAUTIONS

5.1 Personnel and Equipment for Monitoring and Resuscitation

- Prior to the intravenous administration of midazolam in any dose, ensure the immediate availability of oxygen, resuscitative drugs, age- and size-appropriate equipment for bag/valve/mask ventilation and intubation, and skilled personnel for the maintenance of a patent airway and support of ventilation.
- Only personnel trained in the administration of procedural sedation, and not involved in the conduct of the diagnostic or therapeutic procedure, should administer Midazolam in 0.9% Sodium Chloride Injection.
- Administering personnel must be trained in the detection and management of airway obstruction, hypoventilation, and apnea, including the maintenance of a patent airway, supportive ventilation, and cardiovascular resuscitation.
- Continuously monitor patients for early signs of hypoventilation, airway obstruction, or apnea, with means readily available (e.g., pulse oximetry). Hypoventilation, airway obstruction, and apnea can lead to hypoxia and/or cardiac arrest unless effective countermeasures are taken immediately.
- A benzodiazepine reversal agent (i.e., flumazenil) should be immediately available during administration of Midazolam in 0.9% Sodium Chloride Injection.
- Continuously monitor vital signs during the recovery period. Because intravenous midazolam can depress respiration [see Clinical Pharmacology (12)], especially when used concomitantly with opioid agonists and other sedatives [see Dosage and Administration (2)], it should be used for sedation/anxiolysis/amnesia only in the presence of personnel skilled in early detection of hypoventilation, maintaining a patent airway, and supporting ventilation.

5.2 Risks from Concomitant Use with Opioids, Other Sedative Hypnotics, or Other Central Nervous System Depressants

Concomitant use of benzodiazepines and opioids may result in profound sedation, respiratory depression, coma, and death. Monitor patients for respiratory depression and sedation [see Warnings and Precautions (5.2) and Drug Interactions (7.1)].

Titrate the dose of Midazolam in 0.9% Sodium Chloride Injection when administered with opioid analgesics and sedative-hypnotics to the desired clinical response.

Continuously monitor sedated patients for hypotension, airway obstruction, hypoventilation, apnea, and oxygen desaturation. These cardiorespiratory effects may be more likely to occur in patients with obstructive sleep apnea, the elderly, and ASA‑PS III or IV patients.

Concomitant use of barbiturates, alcohol, or other central nervous system depressants may increase the risk of hypoventilation, airway obstruction, desaturation, or apnea and may contribute to profound and/or prolonged drug effect. Narcotic premedication also depresses the ventilatory response to carbon dioxide stimulation.

5.3 Risk of Cardiorespiratory Adverse Reactions

Serious cardiorespiratory adverse reactions have occurred after administration of midazolam. These have included respiratory depression, airway obstruction, oxygen desaturation, apnea, respiratory arrest and/or cardiac arrest, sometimes resulting in death or permanent neurologic injury. There have also been rare reports of hypotensive episodes requiring treatment during or after diagnostic or surgical manipulations particularly in adult or pediatric patients with hemodynamic instability. Hypotension occurred more frequently in the sedation studies in patients premedicated with an opioid. Excessive single doses or rapid intravenous administration may result in respiratory depression, airway obstruction and/or arrest. When used for sedation/anxiolysis/amnesia, midazolam should always be titrated slowly in adult or pediatric patients. Adverse hemodynamic events have been reported in pediatric patients with cardiovascular instability; rapid intravenous administration should also be avoided in this population. Continuously monitor patients for early signs of hypoventilation, airway obstruction, and apnea using capnography, pulse oximetry, and clinical assessment [see Dosage and Administration (2.2)].

5.4 Risk of Paradoxical Behavior

Reactions such as agitation, involuntary movements (including tonic/clonic movements and muscle tremor), hyperactivity and combativeness have been reported in both adult and pediatric patients. These reactions may be due to inadequate or excessive dosing or improper administration of midazolam; however, consideration should be given to the possibility of cerebral hypoxia or true paradoxical reactions. Should such reactions occur, the response to each dose of midazolam and all other drugs, including local anesthetics, should be evaluated before proceeding. Reversal of such responses with flumazenil has been reported in pediatric patients.

5.5 Risk of Dependence and Withdrawal with Long-Term Use of Midazolam in 0.9% Sodium Chloride Injection

The continued use of benzodiazepines for several days to weeks may lead to clinically significant physical dependence. If used for long-term use (i.e., for several days to weeks), abrupt discontinuation or rapid dosage reduction of midazolam, or administration of flumazenil, a benzodiazepine antagonist, may precipitate acute withdrawal reactions, including seizures, which can be life-threatening.

Patients at an increased risk of withdrawal adverse reactions after benzodiazepine discontinuation or rapid dosage reduction include those who take higher dosages (i.e., higher and/or more frequent doses) and those who have had longer durations of use.

After extended therapy, do not abruptly discontinue Midazolam in 0.9% Sodium Chloride Injection. When discontinuing midazolam in a physically-dependent patient, gradually taper the dosage using a tapering schedule that is individualized to the patient [see Dosage and Administration (2.3), Dependence (9.3)].

5.6 Debilitation and Comorbid Considerations

Higher risk adult and pediatric surgical patients, elderly patients and debilitated adult and pediatric patients require lower dosages, whether or not concomitant sedating medications have been administered. Adult or pediatric patients with COPD are unusually sensitive to the respiratory depressant effect of midazolam. Pediatric and adult patients undergoing procedures involving the upper airway such as upper endoscopy or dental care, are particularly vulnerable to episodes of desaturation and hypoventilation due to partial airway obstruction. Adult and pediatric patients with chronic renal failure and patients with congestive heart failure eliminate midazolam more slowly [see Clinical Pharmacology (12.3)]. Because elderly patients frequently have inefficient function of one or more organ systems and because dosage requirements have been shown to decrease with age, reduced initial dosage of midazolam is recommended, and the possibility of profound and/or prolonged effect should be considered.

Do not administer Midazolam in 0.9% Sodium Chloride Injection to adult or pediatric patients in shock or coma, or in acute alcohol intoxication with depression of vital signs. Particular care should be exercised in the use of intravenous midazolam in adult or pediatric patients with uncompensated acute illnesses, such as severe fluid or electrolyte disturbances.

5.7 Risk of Intra-Arterial Injection

There have been limited reports of intra-arterial injection of midazolam. Adverse events have included local reactions, as well as isolated reports of seizure activity in which no clear causal relationship was established. Precautions against unintended intra-arterial injection should be taken. Extravasation should also be avoided.

The safety and efficacy of Midazolam in 0.9% Sodium Chloride Injection following nonintravenous routes of administration have not been established. Midazolam in 0.9% Sodium Chloride Injection should only be administered intravenously.

5.8 Impaired Cognitive Function

Midazolam is associated with a high incidence of partial or complete impairment of recall for the next several hours. The decision as to when patients who have received injectable midazolam, particularly on an outpatient basis, may again engage in activities requiring complete mental alertness, operate hazardous machinery or drive a motor vehicle must be individualized. Gross tests of recovery from the effects of midazolam [see Clinical Pharmacology (12.3)] cannot be relied upon to predict reaction time under stress. It is recommended that no patient operate hazardous machinery or a motor vehicle until the effects of the drug, such as drowsiness, have subsided or until one full day after anesthesia and surgery, whichever is longer. For pediatric patients, particular care should be taken to assure safe ambulation.

5.9 Risk of Hypotension and Seizure in Preterm Infants and Neonates

Rapid injection should be avoided in the neonatal population. Midazolam administered rapidly as an intravenous injection (i.e., less than 2 minutes) has been associated with severe hypotension in neonates, particularly when the patient has also received fentanyl. Likewise, severe hypotension has been observed in neonates receiving a continuous infusion of midazolam who then receive a rapid intravenous injection of fentanyl. Seizures have been reported in several neonates following rapid intravenous administration.

The neonate also has reduced and/or immature organ function and is also vulnerable to profound and/or prolonged respiratory effects of midazolam.

5.10 Neonatal Sedation and Withdrawal Syndrome

Receiving Midazolam in 0.9% Sodium Chloride Injection late in pregnancy can result in sedation (respiratory depression, lethargy, hypotonia) and/or withdrawal symptoms (hyperreflexia, irritability, restlessness, tremors, inconsolable crying, and feeding difficulties) in the neonate. Monitor neonates exposed to Midazolam in 0.9% Sodium Chloride Injection during pregnancy or labor for signs of sedation and manage these neonates accordingly [see Use in Specific Populations (8.1)].

5.11 Pediatric Neurotoxicity

Published animal studies demonstrate that the administration of anesthetic and sedation drugs that block NMDA receptors and/or potentiate GABA activity increase neuronal apoptosis in the developing brain and result in long-term cognitive deficits when used for longer than 3 hours. The clinical significance of these findings is not clear. However, based on the available data, the window of vulnerability to these changes is believed to correlate with exposures in the third trimester of gestation through the first several months of life, but may extend out to approximately three years of age in humans [see Nonclinical Pharmacology (13.2)].

Some published studies in children suggest that similar deficits may occur after repeated or prolonged exposures to anesthetic agents early in life and may result in adverse cognitive or behavioral effects. These studies have substantial limitations, and it is not clear if the observed effects are due to the anesthetic/sedation drug administration or other factors such as the surgery or underlying illness.

Anesthetic and sedation drugs are a necessary part of the care of children needing surgery, other procedures, or tests that cannot be delayed, and no specific medications have been shown to be safer than any other. Decisions regarding the timing of any elective procedures requiring anesthesia should take into consideration the benefits of the procedure weighed against the potential risks.

5.12 Risk of Increased Intraocular Pressure in Patients with Glaucoma

Benzodiazepines, including Midazolam in 0.9% Sodium Chloride Injection, can increase intraocular pressure in patients with glaucoma. Measurements of intraocular pressure in patients without eye disease show a moderate lowering following induction with midazolam. Midazolam in 0.9% Sodium Chloride Injection may be used in patients with open-angle glaucoma only if they are receiving appropriate therapy. Patients with open-angle glaucoma may need to have their ophthalmologic status evaluated following treatment with Midazolam in 0.9% Sodium Chloride Injection. Midazolam in 0.9% Sodium Chloride Injection is contraindicated in patients with narrow-angle glaucoma.

6 ADVERSE REACTIONS

The following serious adverse reactions are discussed in greater detail in other sections:

- Cardiorespiratory Adverse Reactions [see Warnings and Precautions (5.3)]
- Paradoxical Behavior [see Warnings and Precautions (5.4)]
- Dependence and Withdrawal [see Warnings and Precautions (5.5)]
- Impaired Cognitive Function [see Warnings and Precautions (5.8)]
- Hypotension and Seizure in Preterm Infants and Neonates [see Warnings and Precautions (5.9)]
- Neonatal Sedation and Withdrawal Syndrome [see Warnings and Precautions (5.10), Use in Specific Populations (8.1)]
- Pediatric Neurotoxicity [see Warnings and Precautions (5.11)]

The following adverse reactions have been identified from literature or postmarketing reports of midazolam. Because some of these reactions are reported voluntarily from a population of uncertain size, it is not always possible to reliably estimate their frequency or establish a causal relationship to drug exposure.

Fluctuations in vital signs were the most frequently seen findings following parenteral administration of midazolam in adults and included decreased tidal volume and/or respiratory rate decrease (23.3% of patients following intravenous administration) and apnea (15.4% of patients following intravenous administration), as well as variations in blood pressure and pulse rate. The majority of serious adverse reactions, particularly those associated with oxygenation and ventilation, have been reported when midazolam is administered with other medications capable of depressing the central nervous system. The incidence of such events is higher in patients undergoing procedures involving the airway without the protective effect of an endotracheal tube, (e.g., upper endoscopy and dental procedures).

Adults

Table 2: Additional Adverse Reactions Reported Subsequent to Intravenous Administration as a Single Sedative/anxiolytic/amnestic Agent in Adult Patients:

hiccoughs (3.9%) | Local effects at the intravenous site
nausea (2.8%) | tenderness (5.6%)
vomiting (2.6%) | pain during injection (5.0%)
coughing (1.3%) | redness (2.6%)
"oversedation" (1.6%) | induration (1.7%)
headache (1.5%) | phlebitis (0.4%)
drowsiness (1.2%)

Pediatric Patients

The following adverse events related to the use of intravenous midazolam in pediatric patients were reported in the medical literature: desaturation 4.6%, apnea 2.8%, hypotension 2.7%, paradoxical reactions 2.0%, hiccough 1.2%, seizure-like activity 1.1% and nystagmus 1.1%. The majority of airway-related events occurred in patients receiving other CNS depressing medications and in patients where midazolam was not used as a single sedating agent.

Neonates

There have been reports of hypotensive episodes and seizures following the administration of midazolam to neonates, [see Warnings and Precautions (5.9)].

Other Adverse Reactions Occurring at an Incidence of <1.0% Following Intravenous Injection as a Single Sedative/Anxiolytic/Amnesia Agent

Respiratory: Laryngospasm, bronchospasm, dyspnea, hyperventilation, wheezing, shallow respirations, airway obstruction, tachypnea

Cardiovascular: Bigeminy, premature ventricular contractions, vasovagal episode, bradycardia, tachycardia, nodal rhythm

Gastrointestinal: Acid taste, excessive salivation, retching

CNS/Neuromuscular: Retrograde amnesia, euphoria, hallucination, confusion, argumentativeness, nervousness, anxiety, grogginess, restlessness, emergence delirium or agitation, prolonged emergence from anesthesia, dreaming during emergence, sleep disturbance, insomnia, nightmares, athetoid movements, seizure-like activity, ataxia, dizziness, dysphoria, slurred speech, dysphonia, paresthesia

Special Senses: Blurred vision, diplopia, nystagmus, pinpoint pupils, cyclic movements of eyelids, visual disturbance, difficulty focusing eyes, ears blocked, loss of balance, light-headedness

Integumentary: Hive-like elevation at injection site, swelling or feeling of burning, warmth or coldness at injection site

Hypersensitivity: Allergic reactions including anaphylactic reactions, hives, rash, pruritus

Miscellaneous: Yawning, lethargy, chills, weakness, toothache, faint feeling, hematoma

7 DRUG INTERACTIONS

7.1 Opioid Analgesics and Other Sedative Hypnotics

The concomitant use of benzodiazepines and opioids increases the risk of respiratory depression because of actions at different receptor sites in the CNS that control respiration. Benzodiazepines interact at GABAA sites and opioids interact primarily at mu receptors. When benzodiazepines and opioids are combined, the potential for benzodiazepines to significantly worsen opioid-related respiratory depression exists. Monitor patients closely for respiratory depression and sedation.

The sedative effect of intravenous midazolam is accentuated by any concomitantly administered medication which depresses the central nervous system, particularly opioids (e.g., morphine, meperidine and fentanyl) and also secobarbital and droperidol. Consequently, the dosage of midazolam should be adjusted according to the type and amount of concomitant medications administered and the desired clinical response [see Dosage and Administration (2)].

7.2 Cytochrome P450-3A4 Inhibitors

Concomitant administration with drugs that are known to inhibit the P450-3A4 enzyme system, such as cimetidine (not ranitidine), erythromycin, diltiazem, verapamil, ketoconazole and itraconazole, may result in prolonged sedation due to a decrease in plasma clearance of midazolam.

The effect of single oral doses of 800 mg cimetidine and 300 mg ranitidine on steady-state concentrations of midazolam was examined in a randomized crossover study (n=8). Cimetidine increased the mean midazolam steady-state concentration from 57 to 71 ng/mL. Ranitidine increased the mean steady-state concentration to 62 ng/mL. No change in choice reaction time or sedation index was detected after dosing with the H2 receptor antagonists.

In a placebo-controlled study, erythromycin administered as a 500 mg dose, three times a day, for 1 week (n=6), reduced the clearance of midazolam following a single 0.5 mg/kg intravenous dose. The half-life was approximately doubled.

The effects of diltiazem (60 mg three times a day) and verapamil (80 mg three times a day) on the pharmacokinetics and pharmacodynamics of oral midazolam were investigated in a three-way crossover study (n=9). The half-life of midazolam increased from 5 to 7 hours when midazolam was taken in conjunction with verapamil or diltiazem. No interaction was observed in healthy subjects between midazolam and nifedipine.

7.3 Saquinavir

In a placebo-controlled study, saquinavir administered as a 1200 mg dose, tid, for 5 days (n=12), a 56% reduction in the clearance of midazolam following a single 0.05 mg/kg intravenous dose was observed. The half-life was approximately doubled.

7.4 Thiopental

A moderate reduction in induction dosage requirements of thiopental (about 15%) has been noted following use of intramuscular midazolam for premedication in adults.

7.5 Halothane

The intravenous administration of midazolam decreases the minimum alveolar concentration (MAC) of halothane required for general anesthesia. This decrease correlates with the dose of midazolam administered; no similar studies have been carried out in pediatric patients but there is no scientific reason to expect that pediatric patients would respond differently than adults.

7.6 Pancuronium

Although the possibility of minor interactive effects has not been fully studied, midazolam and pancuronium have been used together in patients without noting clinically significant changes in dosage, onset or duration in adults. Midazolam does not protect against the characteristic circulatory changes noted after administration of succinylcholine or pancuronium and does not protect against the increased intracranial pressure noted following administration of succinylcholine. Midazolam does not cause a clinically significant change in dosage, onset or duration of a single intubating dose of succinylcholine; no similar studies have been carried out in pediatric patients but there is no scientific reason to expect that pediatric patients would respond differently than adults.

7.7 Other Drugs Used in the Surgical Setting

No significant adverse interactions with commonly used premedications or drugs used during anesthesia and surgery (including atropine, scopolamine, glycopyrrolate, diazepam, hydroxyzine, d-tubocurarine, succinylcholine and other nondepolarizing muscle relaxants) or topical local anesthetics (including lidocaine, dyclonine HCl and Cetacaine) have been observed in adults or pediatric patients. In neonates, however, severe hypotension has been reported with concomitant administration of fentanyl. This effect has been observed in neonates on an infusion of midazolam who received a rapid injection of fentanyl and in patients on an infusion of fentanyl who have received a rapid injection of midazolam.

7.8 Drug/Laboratory Test Interactions

Midazolam has not been shown to interfere with results obtained in clinical laboratory tests.

8 USE IN SPECIFIC POPULATIONS

8.1 Pregnancy

Risk Summary

Neonates born to mothers using benzodiazepines, including midazolam, late in pregnancy have been reported to experience symptoms of sedation and/or neonatal withdrawal [see Warnings and Precautions (5.10), and Clinical Considerations]. Available data from published observational studies of pregnant women exposed to benzodiazepines do not report a clear association with benzodiazepines and major birth defects (see Data).

Available data from randomized controlled trials, cohort studies and case reports over several decades with midazolam use in pregnant women for anesthesia have not identified a drug-associated risk of major birth defects, miscarriage, or adverse maternal or fetal outcomes. Most of the reported exposures to midazolam occurred at the time of cesarean delivery. Rare case reports of the prolonged use of midazolam in pregnant women for sedation in a critical care setting are insufficient to evaluate for a drug-associated risk of major birth defects, miscarriage or adverse maternal or fetal outcomes (see Data).

In pregnant rats and rabbits, midazolam did not cause adverse effects to the fetus at doses of up to 1.85 times the human induction dose of 0.35 mg/kg based on body surface area comparisons.

Published studies in pregnant primates demonstrate that the administration of anesthetic and sedation drugs that block NMDA receptors and/or potentiate GABA activity during the period of peak brain development increases neuronal apoptosis in the developing brain of the offspring when used for longer than 3 hours. There are no data on pregnancy exposures in primates corresponding to periods prior to the third trimester in humans (see Data).

The background risk of major birth defects and miscarriage for the indicated population is unknown. All pregnancies have a background risk of birth defect, loss, or other adverse outcomes. In the U.S. general population, the estimated background risk of major birth defects and miscarriage in clinically recognized pregnancies is 2 to 4% and 15 to 20%, respectively.

Clinical Considerations

Fetal/Neonatal Adverse Reactions

Benzodiazepines cross the placenta and may produce respiratory depression, hypotonia, and sedation in neonates. Monitor neonates exposed to midazolam during pregnancy or labor for signs of sedation, respiratory depression, hypotonia, and feeding problems. Monitor neonates exposed to midazolam during pregnancy for signs of withdrawal. Manage these neonates accordingly [see Warnings and Precautions (5.2)].

Data

Human Data

Published data from observational studies on the use of benzodiazepines during pregnancy do not report a clear association with benzodiazepines and major birth defects. Although early studies reported an increased risk of congenital malformations with diazepam and chlordiazepoxide, there was no consistent pattern noted. In addition, the majority of more recent case-control and cohort studies of benzodiazepine use during pregnancy, which were adjusted for confounding exposures to alcohol, tobacco and other medications, have not confirmed these findings.

Animal Data

Pregnant rats were treated with midazolam using intravenous doses of 0.2, 1, and 4 mg/kg/day (0.09, 0.46, and 1.85 times the human induction dose of 0.35 mg/kg based on body surface area comparisons) during the period of organogenesis (Gestation Day 7 through 15). Midazolam did not cause adverse effects to the fetus at doses of up to 1.85 times the human induction dose. All doses produced slight to moderate ataxia. The high dose produced a 5% decrease in maternal body weight gain compared to control.

Pregnant rabbits were treated with midazolam using intravenous doses of 0.2, 0.6, and 2 mg/kg/day (0.09, 0.46, and 1.85 times the human induction dose of 0.35 mg/kg based on body surface area comparisons) during the period of organogenesis (Gestation Day 7 to 18). Midazolam did not cause adverse effects to the fetus at doses of up to 1.85 times the human induction dose. The high dose was associated with findings of ataxia and sedation but no evidence of maternal toxicity.

Pregnant rats were administered midazolam using intravenous doses of 0.2, 1, and 4 mg/kg/day (0.09, 0.46, and 1.85 times the human induction dose of 0.35 mg/kg based on body surface area comparisons) during late gestation and through lactation (Gestation Day 15 through Lactation Day 21). All doses produced ataxia. The high dose produced a slight decrease in maternal body weight gain compared to control. There were no clear adverse effects noted in the offspring. The study included no functional assessments of the pups, such as learning and memory testing or reproductive capacity.

In a published study in primates, administration of an anesthetic dose of ketamine for 24 hours on Gestation Day 122 increased neuronal apoptosis in the developing brain of the fetus. In other published studies, administration of either isoflurane or propofol for 5 hours on Gestation Day 120 resulted in increased neuronal and oligodendrocyte apoptosis in the developing brain of the offspring. With respect to brain development, this time period corresponds to the third trimester of gestation in the human. The clinical significance of these findings is not clear; however, studies in juvenile animals suggest neuroapoptosis correlates with long-term cognitive deficits [see Warnings and Precautions (5.8), Use in Specific Populations (8.4), Nonclinical Pharmacology (13.2)].

8.2 Lactation

Risk Summary

There are reports of sedation, poor feeding, and poor weight gain in infants exposed to benzodiazepines through breast milk. Based on data from published studies, midazolam is present in human milk in low levels (see Data). There are no data on the effects of midazolam on milk production.

The developmental and health benefits of breastfeeding should be considered along with the mother’s clinical need for Midazolam in 0.9% Sodium Chloride Injection and any potential adverse effects on the breastfed infant from Midazolam in 0.9% Sodium Chloride Injection or from the underlying maternal condition.

Clinical Considerations

Infants exposed to midazolam through breast milk should be monitored for sedation, poor feeding, and poor weight gain. A lactating woman may consider interrupting breastfeeding and pumping and discarding breast milk during treatment for a range of at least 4 to 8 hours after midazolam administration in order to minimize drug exposure to a breastfed infant.

Data

Published clinical lactation studies describe the presence of midazolam in human milk at low levels 4 to 8 hours after midazolam administration. These lactation studies have limitations including poor methodology and lack of validated analytical methods. Published study guidelines recommend pumping and discarding breast milk for a range of at least 4 to 8 hours after treatment with midazolam. No safety signals have been identified in breastfed infants exposed to midazolam.

8.4 Pediatric Use

The safety and efficacy of midazolam for sedation/anxiolysis/amnesia following continuous infusion have been established in pediatric and neonatal patients. UNLIKE ADULT PATIENTS, PEDIATRIC PATIENTS GENERALLY RECEIVE INCREMENTS OF MIDAZOLAM ON A MG/KG BASIS. As a group, pediatric patients generally require higher dosages of midazolam (mg/kg) than do adults. Younger (less than six years) pediatric patients may require higher dosages (mg/kg) than older pediatric patients, and may require closer monitoring. In obese PEDIATRIC PATIENTS, the dose should be calculated based on ideal body weight. When midazolam is given in conjunction with opioids or other sedatives, the potential for respiratory depression, airway obstruction, or hypoventilation is increased. The health care practitioner who uses this medication in pediatric patients should be aware of and follow accepted professional guidelines for pediatric sedation appropriate to their situation.

Midazolam should not be administered by rapid injection in the neonatal population. Severe hypotension and seizures have been reported following rapid intravenous administration, particularly, with concomitant use of fentanyl.

Animal Data

Published juvenile animal studies demonstrate that the administration of anesthetic and sedation drugs, such as Midazolam in 0.9% Sodium Chloride Injection, that either block NMDA receptors or potentiate the activity of GABA during the period of rapid brain growth or synaptogenesis, results in widespread neuronal and oligodendrocyte cell loss in the developing brain and alterations in synaptic morphology and neurogenesis. Based on comparisons across species, the window of vulnerability to these changes is believed to correlate with exposures in the third trimester of gestation through the first several months of life, but may extend out to approximately 3 years of age in humans.

In primates, exposure to 3 hours of ketamine that produced a light surgical plane of anesthesia did not increase neuronal cell loss, however, treatment regimens of 5 hours or longer of isoflurane increased neuronal cell loss. Data from isoflurane-treated rodents and ketamine-treated primates suggest that the neuronal and oligodendrocyte cell losses are associated with prolonged cognitive deficits in learning and memory. The clinical significance of these nonclinical findings is not known, and healthcare providers should balance the benefits of appropriate anesthesia in pregnant women, neonates, and young children who require procedures with the potential risks suggested by the nonclinical data [see Warnings and Precautions (5.8) and Nonclinical Pharmacology (13.2)].

8.5 Geriatric Use

Because geriatric patients may have altered drug distribution and diminished hepatic and/or renal function, reduced doses of midazolam are recommended. Doses of Midazolam in 0.9% Sodium Chloride Injection should be decreased for elderly and for debilitated patients [see Warnings and Precautions (5.6) and Dosage and Administration (2)] and subjects over 70 years of age may be particularly sensitive. These patients will also probably take longer to recover completely after midazolam administration for the induction of anesthesia. Administration of intravenous midazolam to elderly and/or high-risk surgical patients has been associated with rare reports of death under circumstances compatible with cardiorespiratory depression. In most of these cases, the patients also received other central nervous system depressants capable of depressing respiration, especially opioids [see Dosage and Administration (2)].

Midazolam is known to be substantially excreted by the kidney, and the risk of adverse reactions to this drug may be greater in patients with impaired renal function. Because elderly patients are more likely to have decreased renal function, care should be taken in dose selection, and it may be useful to monitor renal function.

9 DRUG ABUSE AND DEPENDENCE

9.1 Controlled Substance

Midazolam in 0.9% Sodium Chloride Injection contains midazolam, a Schedule IV controlled substance.

9.2 Abuse

Midazolam in 0.9% Sodium Chloride Injection contains the benzodiazepine, midazolam. Benzodiazepines are a class of sedative drugs with a known potential for abuse. Abuse is the intentional, non-therapeutic use of a drug, even once, for its desirable psychological or physiological effects.

Misuse is the intentional use, for therapeutic purposes, of a drug by an individual in a way other than prescribed by a health care provider or for whom it was not prescribed. Drug addiction is a cluster of behavioral, cognitive, and physiological phenomena that may include a strong desire to take the drug, difficulties in controlling drug use (e.g., continuing drug use despite harmful consequences, giving a higher priority to drug use than other activities and obligations), and possible tolerance or physical dependence. Both abuse and misuse may lead to addiction. Midazolam was actively self-administered in primate models used to assess the positive reinforcing effects of psychoactive drugs. Midazolam produced physical dependence of a mild to moderate intensity in cynomolgus monkeys after 5 to 10 weeks of administration. Available data concerning the drug abuse and dependence potential of midazolam suggest that its abuse potential is at least equivalent to that of diazepam.

9.3. Dependence

Midazolam may produce physical dependence after long-term use. Physical dependence is a state that develops as a result of physiological adaptation in response to repeated drug use, manifested by withdrawal signs and symptoms after abrupt discontinuation or a significant dose reduction of a drug. If Midazolam in 0.9% Sodium Chloride Injection is administered long-term (i.e., for several days to weeks), abrupt discontinuation or rapid dosage reduction, or administration of flumazenil, a benzodiazepine antagonist, may precipitate acute withdrawal reactions, including seizures, which can be life-threatening. Patients at an increased risk of withdrawal adverse reactions after benzodiazepine discontinuation or rapid dosage reduction include those who take higher dosages (i.e., higher and/or more frequent doses) and those who have had longer durations of use [see Warnings and Precautions (5.5)].

To reduce the risk of withdrawal reactions, after extended therapy, do not abruptly discontinue Midazolam in 0.9% Sodium Chloride Injection. Gradually taper the dosage using a tapering schedule that is individualized to the patient.

Acute Withdrawal Signs and Symptoms

Acute withdrawal signs and symptoms have included abnormal involuntary movements, anxiety, blurred vision, cognitive disorder, depersonalization, depression, derealization, dizziness, fatigue, gastrointestinal adverse reactions (e.g., nausea, vomiting, diarrhea, weight loss, decreased appetite), headache, hyperacusis, hypertension, irritability, insomnia, memory impairment, muscle pain and stiffness, panic attacks, photophobia, restlessness, tachycardia, and tremor. More severe acute withdrawal signs and symptoms, including life-threatening reactions, have included catatonia, convulsions, delirium tremens, depression, hallucinations, homicidal thoughts, mania, psychosis, and suicidality

Protracted Withdrawal Syndrome

Protracted withdrawal syndrome is characterized by anxiety, cognitive impairment, depression, insomnia, formication, motor symptoms (e.g., weakness, tremor, muscle twitches), paresthesia, and tinnitus that persists beyond 4 to 6 weeks after initial benzodiazepine withdrawal. Protracted withdrawal symptoms may last weeks to more than 12 months.

Tolerance

Midazolam may produce tolerance after long-term use. Tolerance is a physiological state characterized by a reduced response to a drug after repeated administration (i.e., a higher dose of a drug is required to produce the same effect that was once obtained at a lower dose). Tolerance may develop within days or weeks of the therapeutic effects of Midazolam; however, little tolerance develops to the amnestic reactions and other cognitive impairments caused by benzodiazepines.

10 OVERDOSAGE

Clinical Presentation

Overdosage of benzodiazepines is characterized by central nervous system depression ranging from drowsiness to coma. In mild to moderate cases, symptoms can include drowsiness, confusion, dysarthria, lethargy, hypnotic state, diminished reflexes, ataxia, and hypotonia. Rarely, paradoxical or disinhibitory reactions (including agitation, irritability, impulsivity, violent behavior, confusion, restlessness, excitement, and talkativeness) may occur. In severe overdosage cases, patients may develop respiratory depression and coma. Overdosage of benzodiazepines in combination with other CNS depressants (including alcohol and opioids) may be fatal [see Warnings and Precautions (5.2)]. Markedly abnormal (lowered or elevated) blood pressure, heart rate, or respiratory rate raise the concern that additional drugs and/or alcohol are involved in the overdosage. No evidence of specific organ toxicity from midazolam overdosage has been reported.

Management of Overdosage

In managing benzodiazepine overdosage, employ general supportive measures, including intravenous fluids and airway management. Flumazenil, a specific benzodiazepine receptor antagonist indicated for the complete or partial reversal of the sedative effects of benzodiazepines in the management of benzodiazepine overdosage, can lead to withdrawal and adverse reactions, including seizures, particularly in the context of mixed overdosage with drugs that increase seizure risk (e.g., tricyclic and tetracyclic antidepressants) and in patients with long-term benzodiazepine use and physical dependency. The risk of withdrawal seizures with flumazenil use may be increased in patients with epilepsy. Flumazenil is contraindicated in patients who have received a benzodiazepine for control of a potentially life-threatening condition (e.g., status epilepticus). If the decision is made to use flumazenil, it should be used as an adjunct to, not as a substitute for, supportive management of benzodiazepine overdosage. See the flumazenil injection Prescribing Information.

Consider contacting the Poison Help Line (1-800-222-1222) or medical toxicologist for additional overdosage management for recommendations.

11 DESCRIPTION

Midazolam in 0.9% Sodium Chloride Injection is a benzodiazepine available as a sterile, preservative-free, nonpyrogenic solution of midazolam and sodium chloride in water for injection for intravenous use. Each single-dose bag of Midazolam in 0.9% Sodium Chloride Injection contains either 50 mg/50 mL (1 mg/mL) or 100 mg/100 mL (1 mg/mL) of midazolam and 9 mg/mL of sodium chloride in water for injection. Midazolam in Sodium Chloride Injection may contain hydrochloric acid and/or sodium hydroxide for pH adjustment. The pH is approximately 2.5 - 3.5.

Midazolam is a white to light yellow crystalline compound, insoluble in water, freely soluble in ethanol, soluble in methanol. Chemically, midazolam is 8-chloro-6-(2-fluorophenyl)-1-methyl-4H-imidazo[1,5-a][1,4]benzodiazepine. Midazolam has the empirical formula C18H13ClFN3, a calculated molecular weight of 325.77 and the following structural formula:

12 CLINICAL PHARMACOLOGY

12.1 Mechanism of Action

Midazolam is a short-acting benzodiazepine central nervous system (CNS) depressant.

12.2 Pharmacodynamics

The effects of midazolam on the CNS are dependent on the dose administered, the route of administration, and the presence or absence of other medications.

Time to Onset

Sedation in adult and pediatric patients is achieved within 3 to 5 minutes after intravenous injection; the time of onset is affected by total dose administered and the concurrent administration of opioid premedication. Seventy-one percent of the adult patients in endoscopy studies had no recall of introduction of the endoscope; 82% of the patients had no recall of withdrawal of the endoscope. In one study of pediatric patients undergoing lumbar puncture or bone marrow aspiration, 88% of patients had impaired recall vs 9% of the placebo controls. In another pediatric oncology study, 91% of midazolam treated patients were amnestic compared with 35% of patients who had received fentanyl alone.

When midazolam is given intravenous as an anesthetic induction agent, induction of anesthesia occurs in approximately 1.5 minutes when opioid premedication has been administered and in 2 to 2.5 minutes without opioid premedication or other sedative premedication. Some impairment in a test of memory was noted in 90% of the patients studied.

Midazolam, used as directed, does not delay awakening from general anesthesia in adults. Gross tests of recovery after awakening (orientation, ability to stand and walk, suitability for discharge from the recovery room, return to baseline Trieger competency) usually indicate recovery within 2 hours but recovery may take up to 6 hours in some cases. When compared with patients who received thiopental, patients who received midazolam generally recovered at a slightly slower rate. Recovery from anesthesia or sedation for procedures in pediatric patients depends on the dose of midazolam administered, coadministration of other medications causing CNS depression and duration of the procedure.

In patients without intracranial lesions, induction of general anesthesia with intravenous midazolam is associated with a moderate decrease in cerebrospinal fluid pressure (lumbar puncture measurements), similar to that observed following intravenous thiopental. Preliminary data in neurosurgical patients with normal intracranial pressure but decreased compliance (subarachnoid screw measurements) show comparable elevations of intracranial pressure with midazolam and with thiopental during intubation. No similar studies have been reported in pediatric patients.

Intravenous induction doses of midazolam depress the ventilatory response to carbon dioxide stimulation for 15 minutes or more beyond the duration of ventilatory depression following administration of thiopental in adults. Impairment of ventilatory response to carbon dioxide is more marked in adult patients with chronic obstructive pulmonary disease (COPD). Sedation with intravenous midazolam does not adversely affect the mechanics of respiration (resistance, static recoil, most lung volume measurements); total lung capacity and peak expiratory flow decrease significantly but static compliance and maximum expiratory flow at 50% of awake total lung capacity (Vmax) increase.

In cardiac hemodynamic studies in adults, intravenous induction of general anesthesia with midazolam was associated with a slight to moderate decrease in mean arterial pressure, cardiac output, stroke volume and systemic vascular resistance. Slow heart rates (less than 65/minute), particularly in patients taking propranolol for angina, tended to rise slightly; faster heart rates (e.g., 85/minute) tended to slow slightly. In pediatric patients, a comparison of intravenous midazolam (500 mcg/kg) with propofol (2.5 mg/kg) revealed a mean 15% decrease in systolic blood pressure in patients who had received intravenous midazolam vs a mean 25% decrease in systolic blood pressure following propofol.

Plasma Concentration-Efficacy Relationships

Concentration-efficacy relationships (after an intravenous dose) have been demonstrated for a variety of pharmacodynamic measures (eg, reaction time, eye movement, sedation) and are associated with extensive intersubject variability. Logistic regression analysis of sedation scores and steady-state plasma concentration indicated that at plasma concentrations greater than 100 ng/mL there was at least a 50% probability that patients would be sedated, but respond to verbal commands (sedation score=3). At 200 ng/mL there was at least a 50% probability that patients would be asleep, but respond to glabellar tap (sedation score=4).

12.3 Pharmacokinetics

Midazolam's activity is primarily due to the parent drug. Elimination of the parent drug takes place via hepatic metabolism of midazolam to hydroxylated metabolites that are conjugated and excreted in the urine. Six single-dose pharmacokinetic studies involving healthy adults yield pharmacokinetic parameters for midazolam in the following ranges: volume of distribution (Vd), 1.0 to 3.1 L/kg; elimination half-life, 1.8 to 6.4 hours (mean approximately 3 hours); total clearance (Cl), 0.25 to 0.54 L/hr/kg. In a parallel group study, there was no difference in the clearance, in subjects administered 0.15 mg/kg (n=4) and 0.30 mg/kg (n=4) intravenous doses indicating linear kinetics. The clearance was successively reduced by approximately 30% at doses of 0.45 mg/kg (n=4) and 0.6 mg/kg (n=5) indicating non-linear kinetics in this dose range.

Absorption

Following intramuscular administration, Cmax for midazolam and its 1-hydroxy metabolite were approximately one-half of those achieved after intravenous injection.

Distribution

The volume of distribution (Vd) determined from six single-dose pharmacokinetic studies involving healthy adults ranged from 1.0 to 3.1 L/kg. Female gender, old age, and obesity are associated with increased values of midazolam Vd. In humans, midazolam has been shown to cross the placenta and enter into fetal circulation and has been detected in human milk and CSF (see Clinical Pharmacology, Special Populations).

In adults and pediatric patients older than 1 year, midazolam is approximately 97% bound to plasma protein, principally albumin and that for 1-hydroxy metabolite is about 89%.

Elimination

Metabolism

In vitro studies with human liver microsomes indicate that the biotransformation of midazolam is mediated by cytochrome P450-3A4. This cytochrome also appears to be present in gastrointestinal tract mucosa as well as liver. Sixty to seventy percent of the biotransformation products is 1-hydroxy-midazolam (also termed alpha-hydroxy-midazolam) while 4-hydroxy-midazolam constitutes 5% or less. Small amounts of a dihydroxy derivative have also been detected but not quantified. The principal urinary excretion products are glucuronide conjugates of the hydroxylated derivatives.

Drugs that inhibit the activity of cytochrome P450-3A4 may inhibit midazolam clearance and elevate steady-state midazolam concentrations.

Studies of the intravenous administration of 1-hydroxy-midazolam in humans suggest that 1-hydroxy-midazolam is at least as potent as the parent compound and may contribute to the net pharmacologic activity of midazolam. In vitro studies have demonstrated that the affinities of 1- and 4-hydroxy-midazolam for the benzodiazepine receptor are approximately 20% and 7%, respectively, relative to midazolam.

Excretion

Clearance of midazolam is reduced in association with old age, congestive heart failure, liver disease (cirrhosis) or conditions which diminish cardiac output and hepatic blood flow.

The principal urinary excretion product is 1-hydroxy-midazolam in the form of a glucuronide conjugate; smaller amounts of the glucuronide conjugates of 4-hydroxy- and dihydroxy-midazolam are detected as well. The amount of midazolam excreted unchanged in the urine after a single intravenous dose is less than 0.5% (n=5). Following a single intravenous infusion in 5 healthy volunteers, 45% to 57% of the dose was excreted in the urine as 1-hydroxymethyl midazolam conjugate.

Pharmacokinetics-Continuous Infusion

The pharmacokinetic profile of midazolam following continuous infusion, based on 282 adult subjects, has been shown to be similar to that following single-dose administration for subjects of comparable age, gender, body habitus and health status. However, midazolam can accumulate in peripheral tissues with continuous infusion. The effects of accumulation are greater after long-term infusions than after short-term infusions. The effects of accumulation can be reduced by maintaining the lowest midazolam infusion rate that produces satisfactory sedation.

Infrequent hypotensive episodes have occurred during continuous infusion; however, neither the time to onset nor the duration of the episode appeared to be related to plasma concentrations of midazolam or alpha-hydroxy-midazolam. Further, there does not appear to be an increased chance of occurrence of a hypotensive episode with increased loading doses.

Patients with renal impairment may have longer elimination half-lives for midazolam [see Clinical Pharmacology (12.3)].

Specific Populations

Changes in the pharmacokinetic profile of midazolam due to drug interactions, physiological variables, etc., may result in changes in the plasma concentration-time profile and pharmacological response to midazolam in these patients. For example, patients with acute renal failure appear to have a longer elimination half-life for midazolam and may experience delayed recovery [see Clinical Pharmacology (12.3)]. In other groups, the relationship between prolonged half-life and duration of effect has not been established.

Age: Pediatrics and Neonates

In pediatric patients aged 1 year and older, the pharmacokinetic properties following a single dose of midazolam reported in 10 separate studies of midazolam are similar to those in adults. Weight-normalized clearance is similar or higher (0.19 to 0.80 L/hr/kg) than in adults and the terminal elimination half-life (0.78 to 3.3 hours) is similar to or shorter than in adults. The pharmacokinetic properties during and following continuous intravenous infusion in pediatric patients in the operating room as an adjunct to general anesthesia and in the intensive care environment are similar to those in adults.

In seriously ill neonates, however, the terminal elimination half-life of midazolam is substantially prolonged (6.5 to 12.0 hours) and the clearance reduced (0.07 to 0.12 L/hr/kg) compared to healthy adults or other groups of pediatric patients. It cannot be determined if these differences are due to age, immature organ function or metabolic pathways, underlying illness or debility.

Age: Geriatric

In three parallel group studies, the pharmacokinetics of midazolam administered intravenous or intramuscular were compared in young (mean age 29, n=52) and healthy elderly subjects (mean age 73, n=53). Plasma half-life was approximately two-fold higher in the elderly. The mean Vd based on total body weight increased consistently between 15% to 100% in the elderly. The mean Cl decreased approximately 25% in the elderly in two studies and was similar to that of the younger patients in the other.

Obese

In a study comparing normals (n=20) and obese patients (n=20) the mean half-life was greater in the obese group (5.9 vs 2.3 hrs). This was due to an increase of approximately 50% in the Vd corrected for total body weight. The clearance was not significantly different between groups.

Congestive Heart Failure

In patients suffering from congestive heart failure, there appeared to be a two-fold increase in the elimination half-life, a 25% decrease in the plasma clearance and a 40% increase in the volume of distribution of midazolam.

Hepatic Impairment

Midazolam pharmacokinetics were studied after an intravenous single dose (0.075 mg/kg) was administered to 7 patients with biopsy proven alcoholic cirrhosis and 8 control patients. The mean half-life of midazolam increased 2.5-fold in the alcoholic patients. Clearance was reduced by 50% and the Vd increased by 20%. In another study in 21 male patients with cirrhosis, without ascites and with normal kidney function as determined by creatinine clearance, no changes in the pharmacokinetics of midazolam or 1-hydroxy-midazolam were observed when compared to healthy individuals.

Renal Impairment

Patients with renal impairment may have longer elimination half-lives for midazolam and its metabolites which may result in slower recovery.

Midazolam and 1-hydroxy-midazolam pharmacokinetics in 6 ICU patients who developed acute renal failure (ARF) were compared with a normal renal function control group. Midazolam was administered as an infusion (5 to 15 mg/hours). Midazolam clearance was reduced (1.9 vs 2.8 mL/min/kg) and the half-life was prolonged (7.6 vs 13 hours) in the ARF patients. The renal clearance of the 1-hydroxy-midazolam glucuronide was prolonged in the ARF group (4 vs 136 mL/min) and the half-life was prolonged (12 vs >25 hours). Plasma levels accumulated in all ARF patients to about ten times that of the parent drug. The relationship between accumulating metabolite levels and prolonged sedation is unclear.

In a study of chronic renal failure patients (n=15) receiving a single intravenous dose, there was a two-fold increase in the clearance and volume of distribution but the half-life remained unchanged. Metabolite levels were not studied.

13 NONCLINICAL TOXICOLOGY

13.1 Carcinogenesis, Mutagenesis, Impairment of Fertility

Carcinogenesis

Midazolam maleate was administered with diet in mice and rats for 2 years at dosages of 1, 9, or 80 mg/kg/day. In female mice in the highest dose group there was a marked increase in the incidence of hepatic tumors. In high-dose male rats there was a small but statistically significant increase in benign thyroid follicular cell tumors. Dosages of 9 mg/kg/day of midazolam maleate (4 times a human induction dose of 0.35 mg/kg based on body surface area comparison) do not increase the incidence of tumors. The pathogenesis of induction of these tumors is not known. These tumors were found after chronic administration, whereas human use will ordinarily be of single or several doses.

Mutagenesis

Midazolam did not have mutagenic activity in Salmonella typhimurium (5 bacterial strains), Chinese hamster lung cells (V79), human lymphocytes or in the micronucleus test in mice.

Impairment of Fertility

Male rats were treated orally with 1, 4, or 16 mg/kg midazolam beginning 62 days prior to mating with female rats treated with the same doses for 14 days prior to mating to Gestation Day 13 or Lactation Day 21. The high dose produced an equivalent exposure (AUC) as 4 mg/kg intravenous midazolam (1.85 times the human induction dose of 0.35 mg/kg based on body surface area comparison). There were no adverse effects on either male or female fertility noted.

13.2 Animal Toxicology and/or Pharmacology

Published studies in animals demonstrate that the use of anesthetic agents during the period of rapid brain growth or synaptogenesis results in widespread neuronal and oligodendrocyte cell loss in the developing brain and alterations in synaptic morphology and neurogenesis. Based on comparisons across species, the window of vulnerability to these changes is believed to correlate with exposures in the third trimester through the first several months of life, but may extend out to approximately 3 years of age in humans.

In primates, exposure to 3 hours of an anesthetic regimen that produced a light surgical plane of anesthesia did not increase neuronal cell loss, however, treatment regimens of 5 hours or longer increased neuronal cell loss. Data in rodents and in primates suggest that the neuronal and oligodendrocyte cell losses are associated with subtle but prolonged cognitive deficits in learning and memory. The clinical significance of these nonclinical findings is not known, and health care providers should balance the benefits of appropriate anesthesia in neonates and young children who require procedures against the potential risks suggested by the nonclinical data [Warnings and Precautions (5.8)].

16 HOW SUPPLIED/STORAGE AND HANDLING

Midazolam in 0.9% Sodium Chloride Injection is a clear, colorless solution supplied in single-dose bags with an aluminum overwrap available as:

Total Strength per Total Volume | Strength per mL | 10 single-dose bags NDC | Bag and Overwrap NDC
*50 mg per 50 mL | 1 mg/mL | 44567-610-10 | 44567-610-01
100 mg per 100 mL | 1 mg/mL | 44567-611-10 | 44567-611-01

*Partial fill container 50 mL volume in 100 mL container

Store at 20°C to 25°C (68°F to 77°F) [see USP Controlled Room Temperature]. Protect from Freezing. Individual containers may be used up to 48 hours after initial penetration. Discard unused portion.

17 PATIENT COUNSELING INFORMATION

Alcohol and Current Medication
Advise patients to notify their healthcare provider about alcohol or medication use, especially blood pressure medication and antibiotics. Alcohol and other CNS depressants, such as opioid analgesic and benzodiazepines, can have an additive effect when administered with Midazolam in 0.9% Sodium Chloride Injection [see Warnings and Precautions (5.2), Drug Interactions (7.1)].

Effect of Anesthetic and Sedation Drugs on Early Brain Development\
Studies conducted in young animals and children suggest repeated or prolonged use of general anesthetic or sedation drugs in children younger than 3 years may have negative effects on their developing brains. Discuss with parents and caregivers the benefits, risks, and timing and duration of surgery or procedures requiring anesthetic and sedation drugs [see Warnings and Precautions (5.11), Use in Specific Populations (8.1)].

Pregnancy

Advise pregnant females exposed to midazolam late in pregnancy can result in sedation (respiratory depression, lethargy, hypotonia) and/or withdrawal symptoms (hyperreflexia, irritability, restlessness, tremors, inconsolable crying, and feeding difficulties) in newborns. Instruct patients to inform their healthcare provider if they are pregnant during treatment with Midazolam in 0.9% Sodium Chloride Injection [see Warnings and Precautions (5.10), Use in Specific Populations (8.1)].

Lactation

Instruct patients to notify their healthcare provider if they are breastfeeding or intend to breastfeed. Instruct breastfeeding patients receiving midazolam to monitor infants for excessive sedation, poor feeding, and poor weight gain, and to seek medical attention if they notice these signs. A lactating woman may consider pumping and discarding breastmilk for at least 4 to 8 hours after receiving midazolam for sedation or anesthesia to minimize drug exposure to a breastfed infant [see Use in Specific Populations (8.2)].

Residual Sedation and Amnesia
Advise patients that they may experience residual sedation and amnesia. The decision as to when patients who have received injectable midazolam, particularly on an outpatient basis, may again engage in activities requiring complete mental alertness, operate hazardous machinery, or drive a motor vehicle must be individualized [see Warnings and Precautions (5.8)].

Withdrawal

Advise patients that receive midazolam in a critical care setting over an extended period of time that they may experience symptoms of withdrawal following abrupt discontinuation.

Discard unused portion.

Manufactured for:

WG Critical Care, LLC

Paramus, NJ 07652

Made in Switzerland

U.S. Patent Number 10,966,990

Package/Label Display Panel

High Alert Medication

NDC 44567-610-01 Do Not Dilute 50 mL

Midazolam
in 0.9% Sodium Chloride
Injection

50 mg per 50 mL
(1 mg per mL)

Package/Label Display Panel

High Alert Medication

NDC 44567-611-01 Do Not Dilute 100 mL

Midazolam
in 0.9% Sodium Chloride
Injection

100 mg per 100 mL (1 mg per mL)